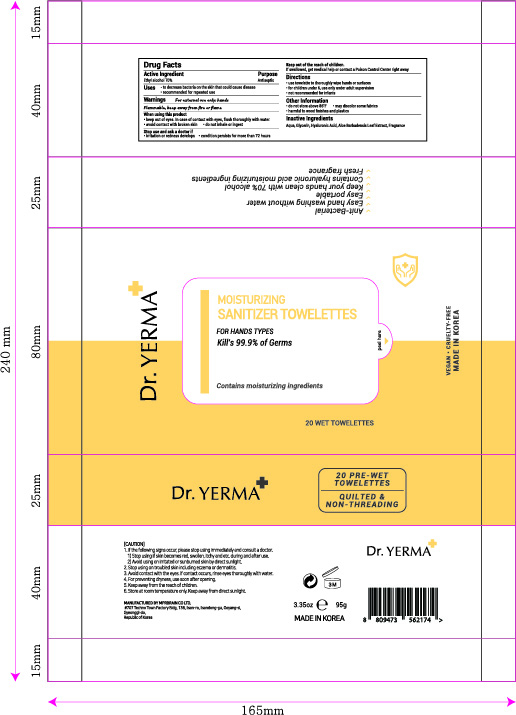 DRUG LABEL: Dr. YERMA MOISTURIZING SANITIZER TOWELETTES
NDC: 74741-7020 | Form: CLOTH
Manufacturer: MPRBRAIN CO.LTD
Category: otc | Type: HUMAN OTC DRUG LABEL
Date: 20200715

ACTIVE INGREDIENTS: ALCOHOL 0.7 1/1 1
INACTIVE INGREDIENTS: ALOE VERA LEAF; GLYCERIN; HYALURONIC ACID; WATER

Dr. YERMA MOISTURIZING SANITIZER TOWELETTES: 20 Towelettes
74741-7020-1